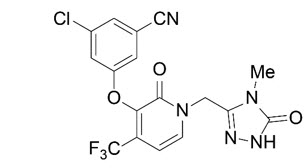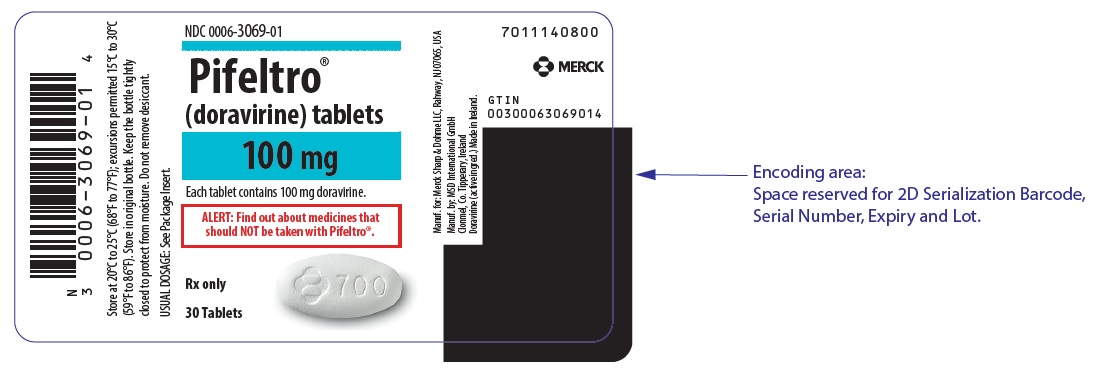 DRUG LABEL: PIFELTRO
NDC: 0006-3069 | Form: TABLET, FILM COATED
Manufacturer: Merck Sharp & Dohme LLC
Category: prescription | Type: HUMAN PRESCRIPTION DRUG LABEL
Date: 20251029

ACTIVE INGREDIENTS: doravirine 100 mg/1 1
INACTIVE INGREDIENTS: silicon dioxide; croscarmellose sodium; hypromellose acetate succinate 06081224 (3 MM2/S); microcrystalline cellulose; magnesium stearate; carnauba wax; hypromellose, unspecified; lactose monohydrate; titanium dioxide; triacetin

HIGHLIGHTS OF PRESCRIBING INFORMATION

These highlights do not include all the information needed to use PIFELTRO safely and effectively. See full prescribing information for PIFELTRO.
PIFELTRO® (doravirine) tablets, for oral use
Initial U.S. Approval: 2018

RECENT MAJOR CHANGES

Warnings and Precautions, Severe Skin Reactions (5.1) | 11/2024

1 INDICATIONS AND USAGE

PIFELTRO, a non-nucleoside reverse transcriptase inhibitor (NNRTI), is indicated in combination with other antiretroviral agents for the treatment of HIV-1 infection in adults and pediatric patients weighing at least 35 kg:

- with no prior antiretroviral treatment history, OR
- to replace the current antiretroviral regimen in those who are virologically-suppressed (HIV-1 RNA less than 50 copies per mL) on a stable antiretroviral regimen with no history of treatment failure and no known substitutions associated with resistance to doravirine. (1)

2 DOSAGE AND ADMINISTRATION

- Recommended dosage: One tablet taken orally once daily with or without food in adults and pediatric patients weighing at least 35 kg. (2.1)
- Dosage adjustment with rifabutin: One tablet taken twice daily (approximately 12 hours apart). (2.2)

3 DOSAGE FORMS AND STRENGTHS

- Tablets: 100 mg doravirine. (3)

4 CONTRAINDICATIONS

- PIFELTRO is contraindicated when co-administered with drugs that are strong cytochrome P450 (CYP)3A enzyme inducers as significant decreases in doravirine plasma concentrations may occur, which may decrease the effectiveness of PIFELTRO. (4)

5 WARNINGS AND PRECAUTIONS

- Severe skin reactions, including Stevens-Johnson syndrome (SJS)/toxic epidermal necrolysis (TEN), have been reported during the postmarketing experience with doravirine-containing regimens. Discontinue PIFELTRO, and other medications known to be associated with severe skin reactions, immediately if a painful rash with mucosal involvement or a progressive severe rash develops, and closely monitor clinical status. (5.1)
- Monitor for Immune Reconstitution Syndrome. (5.3)

6 ADVERSE REACTIONS

Most common adverse reactions (incidence greater than or equal to 5%, all grades) are nausea, dizziness, headache, fatigue, diarrhea, abdominal pain, and abnormal dreams. (6.1)

To report SUSPECTED ADVERSE REACTIONS, contact Merck Sharp & Dohme LLC at 1-877-888-4231 or FDA at 1-800-FDA-1088 or www.fda.gov/medwatch .

7 DRUG INTERACTIONS

Consult the full prescribing information prior to and during treatment for important potential drug-drug interactions. (4, 5.2, 7)

8 USE IN SPECIFIC POPULATIONS

- Pediatrics: Not recommended for patients weighing less than 35 kg. (8.4)

FULL PRESCRIBING INFORMATION

1 INDICATIONS AND USAGE

PIFELTRO® is indicated in combination with other antiretroviral agents for the treatment of HIV-1 infection in adults and pediatric patients weighing at least 35 kg:

- with no prior antiretroviral treatment history; OR
- to replace the current antiretroviral regimen in those who are virologically-suppressed (HIV-1 RNA less than 50 copies per mL) on a stable antiretroviral regimen with no history of treatment failure and no known substitutions associated with resistance to doravirine [see Clinical Studies (14)].

2 DOSAGE AND ADMINISTRATION

2.1 Recommended Dosage

The recommended dosage regimen of PIFELTRO in adults and pediatric patients weighing at least 35 kg is one 100 mg tablet taken orally once daily with or without food [see Clinical Pharmacology (12.3)].

2.2 Dosage Adjustment with Rifabutin

If PIFELTRO is co-administered with rifabutin, increase PIFELTRO dosage to one tablet twice daily (approximately 12 hours apart) for the duration of rifabutin co-administration [see Drug Interactions (7.1) and Clinical Pharmacology (12.3)].

3 DOSAGE FORMS AND STRENGTHS

PIFELTRO film-coated tablets are white, oval-shaped tablets, debossed with the corporate logo and 700 on one side and plain on the other side. Each tablet contains 100 mg doravirine.

4 CONTRAINDICATIONS

PIFELTRO is contraindicated when co-administered with drugs that are strong cytochrome P450 (CYP)3A enzyme inducers as significant decreases in doravirine plasma concentrations may occur, which may decrease the effectiveness of PIFELTRO [see Warnings and Precautions (5.2), Drug Interactions (7.1), and Clinical Pharmacology (12.3)]. These drugs include, but are not limited to, the following:

- the anticonvulsants carbamazepine, oxcarbazepine, phenobarbital, phenytoin
- the androgen receptor inhibitor enzalutamide
- the antimycobacterials rifampin, rifapentine
- the cytotoxic agent mitotane
- St. John's wort (Hypericum perforatum)

5 WARNINGS AND PRECAUTIONS

5.1 Severe Skin Reactions

Severe skin reactions, including Stevens-Johnson syndrome (SJS)/toxic epidermal necrolysis (TEN), have been reported during the postmarketing experience with doravirine-containing regimens [see Adverse Reactions (6.2)]. Discontinue PIFELTRO, and other medications known to be associated with severe skin reactions, immediately if a painful rash with mucosal involvement or a progressive severe rash develops. Clinical status should be closely monitored, and appropriate therapy should be initiated.

5.2 Risk of Adverse Reactions or Loss of Virologic Response Due to Drug Interactions

The concomitant use of PIFELTRO and certain other drugs may result in known or potentially significant drug interactions, some of which may lead to loss of therapeutic effect of PIFELTRO and possible development of resistance [see Dosage and Administration (2.2), Contraindications (4) and Drug Interactions (7.1)].

See Table 6 for steps to prevent or manage these possible and known significant drug interactions, including dosing recommendations. Consider the potential for drug interactions prior to and during PIFELTRO therapy, review concomitant medications during PIFELTRO therapy, and monitor for adverse reactions.

5.3 Immune Reconstitution Syndrome

Immune reconstitution syndrome has been reported in patients treated with combination antiretroviral therapy. During the initial phase of combination antiretroviral treatment, patients whose immune system responds may develop an inflammatory response to indolent or residual opportunistic infections (such as Mycobacterium avium infection, cytomegalovirus, Pneumocystis jirovecii pneumonia (PCP), or tuberculosis), which may necessitate further evaluation and treatment.

Autoimmune disorders (such as Graves' disease, polymyositis, Guillain-Barré syndrome, and autoimmune hepatitis) have also been reported to occur in the setting of immune reconstitution; however, the time to onset is more variable and can occur many months after initiation of treatment.

6 ADVERSE REACTIONS

The following adverse reactions are discussed in other sections of the labeling:

- Immune Reconstitution Syndrome [see Warnings and Precautions (5.3)]

6.1 Clinical Trials Experience

Because clinical trials are conducted under widely varying conditions, adverse reaction rates observed in the clinical trials of a drug cannot be directly compared to rates in the clinical trials of another drug and may not reflect the rates observed in practice.

Adverse Reactions in Adults with No Antiretroviral Treatment History

The safety assessment of PIFELTRO used in combination with other antiretroviral agents is based on Week 96 data from two Phase 3, randomized, international, multicenter, double-blind, active-controlled trials (DRIVE-FORWARD (Protocol 018) and DRIVE-AHEAD (Protocol 021)).

In DRIVE-FORWARD, 766 adult participants received either PIFELTRO 100 mg (n=383) or darunavir 800 mg + ritonavir 100 mg (DRV+r) (n=383) once daily, each in combination with emtricitabine/tenofovir disoproxil fumarate (FTC/TDF) or abacavir/lamivudine (ABC/3TC). By Week 96, 2% in the PIFELTRO group and 3% in the DRV+r group had adverse events leading to discontinuation of study medication.

In DRIVE-AHEAD, 728 adult participants received either DELSTRIGO [doravirine (DOR)/3TC/TDF] (n=364) or efavirenz (EFV)/FTC/TDF once daily (n=364). By Week 96, 3% in the DELSTRIGO group and 7% in the EFV/FTC/TDF group had adverse events leading to discontinuation of study medication.

Adverse reactions reported in greater than or equal to 5% of participants in any treatment group in DRIVE-FORWARD and DRIVE-AHEAD are presented in Table 1.

Table 1: Adverse Reactions [Frequencies of adverse reactions are based on all adverse events attributed to trial drugs by the investigator.] (All Grades) Reported in ≥5% [No adverse reactions of Grade 2 or higher (moderate or severe) occurred in ≥ 2% of participants treated with doravirine.] of Participants in Any Treatment Group in Adults with No Antiretroviral Treatment History in DRIVE-FORWARD and DRIVE-AHEAD (Week 96)
 | DRIVE-FORWARD |  | DRIVE-AHEAD
 | PIFELTRO+2 NRTIs [NRTI = nucleoside reverse transcriptase inhibitor.] Once Daily N=383 | DRV+r+2 NRTIs Once Daily N=383 | DELSTRIGO Once Daily N=364 | EFV/FTC/TDF Once Daily N=364
Nausea | 7% | 8% | 5% | 7%
Headache | 6% | 3% | 4% | 5%
Fatigue | 6% | 3% | 4% | 4%
Diarrhea | 6% | 13% | 4% | 6%
Abdominal Pain | 5% | 2% | 1% | 2%
Dizziness | 3% | 2% | 7% | 32%
Rash | 2% | 3% | 2% | 12%
Abnormal Dreams | 1% | <1% | 5% | 10%
Insomnia | 1% | 2% | 4% | 5%
Somnolence | 0% | <1% | 3% | 7%
NRTIs = FTC/TDF or ABC/3TC.
Fatigue: includes fatigue, asthenia, malaise
Abdominal Pain: includes abdominal discomfort, abdominal pain, abdominal pain lower, abdominal pain upper, epigastric discomfort
Rash: includes rash, rash erythematous, rash generalized, rash macular, rash maculo-papular, rash papular, rash pruritic, rash pustular

The majority (77%) of adverse reactions associated with doravirine occurred at severity Grade 1 (mild).

Neuropsychiatric Adverse Events

For DRIVE-AHEAD, the analysis of participants with neuropsychiatric adverse events by Week 48 is presented in Table 2. The proportion of participants who reported one or more neuropsychiatric adverse events was 24% and 57% in the DELSTRIGO and EFV/FTC/TDF groups, respectively.

A statistically significantly lower proportion of DELSTRIGO-treated participants compared to EFV/FTC/TDF-treated participants reported neuropsychiatric adverse events by Week 48 in the three pre-specified categories of dizziness, sleep disorders and disturbances, and altered sensorium.

Table 2: DRIVE-AHEAD - Analysis of Participants with Neuropsychiatric Adverse Events [All causality and all grade events were included in the analysis.] (Week 48)
 | DELSTRIGO Once Daily N=364 | EFV/FTC/TDF Once Daily N=364 | Treatment Difference DELSTRIGO - EFV/FTC/TDF Estimate (95% CI) [The 95% CIs were calculated using Miettinen and Nurminen's method. Categories pre-specified for statistical testing were dizziness (p <0.001), sleep disorders and disturbances (p <0.001), and altered sensorium (p=0.033).]
Sleep disorders and disturbances [Predefined using MedDRA preferred terms, including: abnormal dreams, hyposomnia, initial insomnia, insomnia, nightmare, sleep disorder, somnambulism.] | 12% | 26% | -13.5 (-19.1, -7.9)
Dizziness | 9% | 37% | -28.3 (-34.0, -22.5)
Altered sensorium [Predefined using MedDRA preferred terms, including: altered state of consciousness, lethargy, somnolence, syncope.] | 4% | 8% | -3.8 (-7.6, -0.3)

Neuropsychiatric adverse events in the pre-defined category of depression and suicide/self-injury were reported in 4% and 7% of participants, in the DELSTRIGO and EFV/FTC/TDF groups, respectively.

In DRIVE-AHEAD through 48 weeks of treatment, the majority of participants who reported neuropsychiatric adverse events reported events that were mild to moderate in severity (97% [83/86] and 96% [198/207], in the DELSTRIGO and EFV/FTC/TDF groups, respectively) and the majority of participants reported these events in the first 4 weeks of treatment (72% [62/86] in the DELSTRIGO group and 86% [177/207] in the EFV/FTC/TDF group).

Neuropsychiatric adverse events led to treatment discontinuation in 1% (2/364) and 1% (5/364) of participants in the DELSTRIGO and EFV/FTC/TDF groups, respectively. The proportion of participants who reported neuropsychiatric adverse events through Week 4 was 17% (62/364) in the DELSTRIGO group and 49% (177/364) in the EFV/FTC/TDF group. At Week 48, the prevalence of neuropsychiatric adverse events was 12% (44/364) in the DELSTRIGO group and 22% (81/364) in the EFV/FTC/TDF group. At Week 96, the prevalence of neuropsychiatric adverse events was 13% (47/364) in the DELSTRIGO group and 23% (82/364) in the EFV/FTC/TDF group.

Laboratory Abnormalities

The percentages of participants with selected laboratory abnormalities (that represent a worsening from baseline) who were treated with PIFELTRO or DRV+r in DRIVE-FORWARD, or DELSTRIGO or EFV/FTC/TDF in DRIVE-AHEAD are presented in Table 3.

Table 3: Selected Laboratory Abnormalities Reported in Adult Participants with No Antiretroviral Treatment History in DRIVE-FORWARD and DRIVE-AHEAD (Week 96)
 | DRIVE-FORWARD |  | DRIVE-AHEAD
Laboratory Parameter Preferred Term (Unit)/Limit | PIFELTRO+2 NRTIs Once Daily N=383 | DRV+r+2 NRTIs Once Daily N=383 | DELSTRIGO Once Daily N=364 | EFV/FTC/TDF Once Daily N=364
Blood Chemistry
Total bilirubin (mg/dL)
1.1 - < 1.6 × ULN | 6% | 2% | 5% | 0%
1.6 - <2.6 × ULN | 2% | <1% | 2% | 0%
≥2.6 × ULN | <1% | 0% | 1% | <1%
Creatinine (mg/dL)
>1.3 - 1.8 × ULN or Increase of >0.3 mg/dL above baseline | 4% | 6% | 3% | 2%
>1.8 × ULN or Increase of ≥1.5 × above baseline | 4% | 4% | 3% | 2%
Aspartate aminotransferase (IU/L)
2.5 - <5.0 × ULN | 5% | 4% | 3% | 3%
≥5.0 × ULN | 2% | 2% | 1% | 4%
Alanine aminotransferase (IU/L)
2.5 - <5.0 × ULN | 4% | 2% | 4% | 4%
≥5.0 × ULN | 2% | 3% | 1% | 3%
Alkaline phosphatase (IU/L)
2.5 - <5.0 × ULN | <1% | 1% | <1% | 1%
≥5.0 × ULN | 0% | <1% | 0% | <1%
Lipase
1.5 - <3.0 × ULN | 7% | 6% | 6% | 4%
≥3.0 × ULN | 3% | 4% | 2% | 3%
Creatine kinase (IU/L)
6.0 - <10.0 × ULN | 3% | 3% | 3% | 3%
≥10.0 × ULN | 5% | 6% | 4% | 6%
Cholesterol, fasted (mg/dL)
≥300 mg/dL | 0% | 1% | 1% | <1%
LDL cholesterol, fasted (mg/dL)
≥190 mg/dL | <1% | 4% | <1% | 2%
Triglycerides, fasted (mg/dL)
>500 mg/dL | 1% | 2% | 1% | 3%
Each participant is only counted once per parameter at the highest toxicity grade. Only participants with a baseline value and at least one on-treatment value for a given laboratory parameter are included.
ULN = Upper limit of normal range.
Note: NRTIs = FTC/TDF or ABC/3TC.

Change in Lipids from Baseline

For DRIVE-FORWARD and DRIVE-AHEAD, changes from baseline at Week 48 in LDL-cholesterol, non-HDL-cholesterol, total cholesterol, triglycerides, and HDL-cholesterol are shown in Table 4. Changes from baseline at Week 96 were similar to those seen at Week 48.

The LDL and non-HDL comparisons were pre-specified and are summarized in Table 4. The differences were statistically significant, showing superiority for doravirine for both parameters. The clinical benefit of these findings has not been demonstrated.

Table 4: Mean Change from Baseline in Fasting Lipids in Adult Participants with No Antiretroviral Treatment History in DRIVE-FORWARD and DRIVE-AHEAD (Week 48)
 | DRIVE-FORWARD
 | PIFELTRO+2 NRTIs Once Daily N=320 |  | DRV+r+2 NRTIs Once Daily N=311
Laboratory Parameter Preferred Term | Baseline | Change | Baseline | Change | Difference Estimates (95% CI)
LDL-Cholesterol (mg/dL) [p-values for the pre-specified hypothesis testing for treatment difference were <0.0001 in both DRIVE-FORWARD and DRIVE-AHEAD.] | 91.4 | -4.6 | 92.3 | 9.5 | -14.4 (-18.0, -10.8)
Non-HDL Cholesterol (mg/dL) | 113.6 | -5.4 | 114.5 | 13.7 | -19.4 (-23.4, -15.4)
Total Cholesterol (mg/dL) [Not pre-specified for hypothesis testing.] | 157.2 | -1.4 | 157.8 | 18.0 | -
Triglycerides (mg/dL) | 111.0 | -3.1 | 113.7 | 24.5 | -
HDL-Cholesterol (mg/dL) | 43.6 | 4.0 | 43.3 | 4.3 | -
DRIVE-AHEAD
 | DELSTRIGO Once Daily N=320 |  | EFV/FTC/TDF Once Daily N=307
Laboratory Parameter Preferred Term | Baseline | Change | Baseline | Change | Difference Estimates (95% CI)
LDL-Cholesterol (mg/dL) | 91.7 | -2.1 | 91.3 | 8.3 | -10.2 (-13.8, -6.7)
Non-HDL Cholesterol (mg/dL) | 114.7 | -4.1 | 115.3 | 12.7 | -16.9 (-20.8, -13.0)
Total Cholesterol (mg/dL) | 156.8 | -2.2 | 156.8 | 21.1 | -
Triglycerides (mg/dL) | 118.7 | -12.0 | 122.6 | 21.6 | -
HDL-Cholesterol (mg/dL) | 42.1 | 1.8 | 41.6 | 8.4 | -
Participants on lipid-lowering agents at baseline were excluded from these analyses (in DRIVE-FORWARD: PIFELTRO n=12 and DRV+r n=14; in DRIVE-AHEAD: DELSTRIGO n=15 and EFV/FTC/TDF n=10). Participants initiating a lipid-lowering agent post-baseline had their last fasted on-treatment value (prior to starting the agent) carried forward (in DRIVE-FORWARD: PIFELTRO n=6 and DRV+r n=4; in DRIVE-AHEAD: DELSTRIGO n=3 and EFV/FTC/TDF n=8).

Adverse Reactions in Virologically-Suppressed Adults

The safety of DELSTRIGO in virologically-suppressed adults was based on Week 48 data from 670 participants in the DRIVE-SHIFT trial (Protocol 024), a randomized, international, multicenter, open-label trial in which virologically-suppressed participants were switched from a baseline regimen consisting of two NRTIs in combination with a protease inhibitor (PI) plus either ritonavir or cobicistat, or elvitegravir plus cobicistat, or a non-nucleoside reverse transcriptase inhibitor (NNRTI) to DELSTRIGO. Overall, the safety profile in virologically-suppressed adult participants was similar to that in participants with no antiretroviral treatment history.

Laboratory Abnormalities

Serum ALT and AST Elevations: In the DRIVE-SHIFT trial, 22% and 16% of participants in the immediate switch group experienced ALT and AST elevations greater than 1.25 × ULN, respectively, through 48 weeks on DELSTRIGO. For these ALT and AST elevations, no apparent patterns with regard to time to onset relative to switch were observed. One percent of participants had ALT or AST elevations greater than 5 × ULN through 48 weeks on DELSTRIGO. The ALT and AST elevations were generally asymptomatic and not associated with bilirubin elevations. In comparison, 4% and 4% of participants in the delayed switch group experienced ALT and AST elevations of greater than 1.25 × ULN through 24 weeks on their baseline regimen.

Change in Lipids from Baseline

Changes from baseline at Week 24 in LDL-cholesterol, non-HDL-cholesterol, total cholesterol, triglycerides, and HDL-cholesterol in participants on a PI plus ritonavir-based regimen at baseline are shown in Table 5. The LDL and non-HDL comparisons were pre-specified, and the differences were statistically significant, showing superiority for an immediate switch to DELSTRIGO for both parameters. The clinical benefit of these findings has not been demonstrated.

Table 5: Mean Change from Baseline in Fasting Lipids in Adult Virologically-Suppressed Participants on a PI plus Ritonavir-based Regimen at Baseline in DRIVE-SHIFT (Week 24)
Laboratory Parameter Preferred Term | DELSTRIGO (Week 0-24) Once Daily N=244 |  | PI+ritonavir (Week 0-24) Once Daily N=124 |  | Difference Estimates
 | Baseline | Change | Baseline | Change | Difference (95% CI)
LDL-Cholesterol (mg/dL) [p-value for the pre-specified hypothesis testing for treatment difference was <0.0001.] | 108.7 | -16.3 | 110.5 | -2.6 | -14.5 (-18.9, -10.1)
Non-HDL Cholesterol (mg/dL) | 138.6 | -24.8 | 138.8 | -2.1 | -22.8 (-27.9, -17.7)
Total Cholesterol (mg/dL) [Not pre-specified for hypothesis testing.] | 188.5 | -26.1 | 187.4 | -0.2 | -
Triglycerides (mg/dL) | 153.1 | -44.4 | 151.4 | -0.4 | -
HDL-Cholesterol (mg/dL) | 50.0 | -1.3 | 48.5 | 1.9 | -
Participants on lipid-lowering agents at baseline were excluded from these analyses (DELSTRIGO n=26 and PI+ritonavir n=13).
Participants initiating a lipid-lowering agent post-baseline had their last fasted on-treatment value (prior to starting the agent) carried forward (DELSTRIGO n=4 and PI+ritonavir n=2).

Adverse Reactions in Pediatric Participants

The safety of doravirine as a component of DELSTRIGO was evaluated in 45 virologically-suppressed or treatment-naïve pediatric participants 12 to less than 18 years of age living with HIV through Week 24 in an open-label trial (IMPAACT 2014 (Protocol 027)) [see Clinical Studies (14.3)]. The safety profile in pediatric participants was similar to that in adults. There were no serious or Grade 3 or 4 adverse reactions. No participants discontinued due to an adverse event.

6.2 Postmarketing Experience

The following adverse reactions have been identified during postmarketing experience in patients receiving doravirine-containing regimens. Because postmarketing reactions are reported voluntarily from a population of uncertain size, it is not always possible to reliably estimate their frequency or establish a causal relationship to drug exposure.

Skin and Subcutaneous Tissue Disorders: Stevens-Johnson syndrome (SJS)/toxic epidermal necrolysis (TEN)

Hepatobiliary Disorders: hepatitis

Investigations: hepatic enzyme increased

7 DRUG INTERACTIONS

7.1 Effect of Other Drugs on PIFELTRO

Co-administration of PIFELTRO with a CYP3A inducer decreases doravirine plasma concentrations, which may reduce PIFELTRO efficacy [see Contraindications (4), Warnings and Precautions (5.2), and Clinical Pharmacology (12.3)]. Co-administration of PIFELTRO and drugs that are inhibitors of CYP3A may result in increased plasma concentrations of doravirine.

Table 6 shows significant drug interactions with PIFELTRO.

Table 6: Drug Interactions with PIFELTRO [This table is not all inclusive.]
Concomitant Drug Class: Drug Name | Effect on Concentration | Clinical Comment
Androgen Receptors
enzalutamide | ↓ doravirine | Co-administration is contraindicated with enzalutamide. At least a 4-week cessation period is recommended prior to initiation of PIFELTRO.
Anticonvulsants
carbamazepine oxcarbazepine phenobarbital phenytoin | ↓ doravirine | Co-administration is contraindicated with these anticonvulsants. At least a 4-week cessation period is recommended prior to initiation of PIFELTRO.
Antimycobacterials
rifampin [The interaction between PIFELTRO and the concomitant drug was evaluated in a clinical study.] rifapentine | ↓ doravirine | Co-administration is contraindicated with rifampin or rifapentine. At least a 4-week cessation period is recommended prior to initiation of PIFELTRO.
rifabutin | ↓ doravirine | Increase PIFELTRO dosage to one tablet twice daily when co-administered with rifabutin [see Dosage and Administration (2.2)].
Cytotoxic Agents
mitotane | ↓ doravirine | Co-administration is contraindicated with mitotane. At least a 4-week cessation period is recommended prior to initiation of PIFELTRO.
HIV Antiviral Agents
efavirenz etravirine nevirapine | ↓ doravirine | Use with efavirenz, etravirine, or nevirapine is not recommended.
Herbal Products
St. John's wort | ↓ doravirine | Co-administration is contraindicated with St. John's wort. At least a 4-week cessation period is recommended prior to initiation of PIFELTRO.
↑ = increase, ↓ = decrease
All other drug-drug interactions shown are anticipated based on the known metabolic and elimination pathways.

No clinically significant changes in concentration were observed for doravirine when co-administered with the following agents: dolutegravir, TDF, lamivudine, elbasvir and grazoprevir, ledipasvir and sofosbuvir, ritonavir, ketoconazole, aluminum hydroxide/magnesium hydroxide/simethicone containing antacid, pantoprazole, and methadone [see Clinical Pharmacology (12.3)].

7.2 Effect of PIFELTRO on Other Drugs

No clinically significant changes in concentration were observed for the following agents when co-administered with doravirine: dolutegravir, lamivudine, TDF, elbasvir and grazoprevir, ledipasvir and sofosbuvir, atorvastatin, an oral contraceptive containing ethinyl estradiol and levonorgestrel, metformin, methadone, and midazolam [see Clinical Pharmacology (12.3)].

8 USE IN SPECIFIC POPULATIONS

8.1 Pregnancy

Pregnancy Exposure Registry

There is a pregnancy exposure registry that monitors pregnancy outcomes in individuals exposed to PIFELTRO during pregnancy. Healthcare providers are encouraged to register patients by calling the Antiretroviral Pregnancy Registry (APR) at 1-800-258-4263.

Risk Summary

No adequate human data are available to establish whether or not PIFELTRO poses a risk to pregnancy outcomes. In animal reproduction studies, no adverse developmental effects were observed when doravirine was administered at exposures ≥8 times the exposure in humans at the recommended human dose (RHD) of PIFELTRO (see Data).

The background rate of major birth defects is 2.7% in a U.S. reference population of the Metropolitan Atlanta Congenital Defects Program (MACDP). The rate of miscarriage is not reported in the APR. The estimated background rate of miscarriage in the clinically recognized pregnancies in the U.S. general population is 15-20%. Methodological limitations of the APR include the use of MACDP as the external comparator group. The MACDP population is not disease-specific, evaluates individuals and infants from the limited geographic area, and does not include outcomes for births that occurred at less than 20 weeks gestation.

Data

Animal Data

Doravirine was administered orally to pregnant rabbits (up to 300 mg/kg/day on gestation days (GD) 7 to 20) and rats (up to 450 mg/kg/day on GD 6 to 20 and separately from GD 6 to lactation/postpartum day 20). No significant toxicological effects on embryo-fetal (rats and rabbits) or pre/post-natal (rats) development were observed at exposures (AUC) approximately 9 times (rats) and 8 times (rabbits) the exposure in humans at the RHD. Doravirine was transferred to the fetus through the placenta in embryo-fetal studies, with fetal plasma concentrations of up to 40% (rabbits) and 52% (rats) that of maternal concentrations observed on GD 20.

8.2 Lactation

Risk Summary

It is unknown whether doravirine is present in human milk, affects human milk production, or has effects on the breastfed infant. Doravirine is present in the milk of lactating rats (see Data). Potential risks of breastfeeding include: (1) HIV-1 transmission (in HIV-1-negative infants), (2) developing viral resistance (in HIV-1-positive infants), and (3) serious adverse reactions in a breastfed infant similar to those seen in adults.

Data

Doravirine was excreted into the milk of lactating rats following oral administration (450 mg/kg/day) from GD 6 to lactation day 14, with milk concentrations approximately 1.5 times that of maternal plasma concentrations observed 2 hours post dose on lactation day 14.

8.4 Pediatric Use

The safety and efficacy of PIFELTRO for the treatment of HIV-1 infection have been established in pediatric patients weighing at least 35 kg [see Indications and Usage (1) and Dosage and Administration (2.1)].

Use of PIFELTRO in this group is supported by evidence from adequate and well-controlled trials in adults and an open-label trial in virologically-suppressed or treatment-naïve pediatric participants 12 to less than 18 years of age. The safety, efficacy, and exposure of doravirine in these pediatric participants were similar to that in adults [see Adverse Reactions (6.1), Clinical Pharmacology (12.3), and Clinical Studies (14.3)].

Safety and efficacy of PIFELTRO in pediatric patients weighing less than 35 kg have not been established.

8.5 Geriatric Use

Clinical trials of PIFELTRO did not include sufficient numbers of participants aged 65 years and over to determine whether they respond differently from younger participants. In general, caution should be exercised in the administration of PIFELTRO in elderly patients, reflecting the greater frequency of decreased hepatic, renal, or cardiac function, and of concomitant disease or other drug therapy [see Clinical Pharmacology (12.3)].

8.6 Renal Impairment

No dosage adjustment of PIFELTRO is required in patients with mild, moderate, or severe renal impairment. PIFELTRO has not been adequately studied in patients with end-stage renal disease and has not been studied in dialysis patients [see Clinical Pharmacology (12.3)].

8.7 Hepatic Impairment

No dosage adjustment of PIFELTRO is required in patients with mild (Child-Pugh Class A) or moderate (Child-Pugh Class B) hepatic impairment. PIFELTRO has not been studied in patients with severe hepatic impairment (Child-Pugh Class C) [see Clinical Pharmacology (12.3)].

11 DESCRIPTION

PIFELTRO is a film-coated tablet containing doravirine for oral administration.

Doravirine is an HIV-1 non-nucleoside reverse transcriptase inhibitor (NNRTI).

Each tablet contains 100 mg of doravirine as the active ingredient. The tablets include the following inactive ingredients: colloidal silicon dioxide, croscarmellose sodium, hypromellose acetate succinate, lactose monohydrate, magnesium stearate, and microcrystalline cellulose. The tablets are film coated with a coating material containing the following inactive ingredients: hypromellose, lactose monohydrate, titanium dioxide, and triacetin. The coated tablets are polished with carnauba wax.

The chemical name for doravirine is 3-chloro-5-[[1-[(4,5-dihydro-4-methyl-5-oxo-1H-1,2,4-triazol-3-yl)methyl]-1,2-dihydro-2-oxo-4-(trifluoromethyl)-3-pyridinyl]oxy]benzonitrile.

It has a molecular formula of C17H11ClF3N5O3 and a molecular weight of 425.75.

It has the following structural formula:

Doravirine is practically insoluble in water.

12 CLINICAL PHARMACOLOGY

12.1 Mechanism of Action

Doravirine is an antiretroviral drug [see Microbiology (12.4)].

12.2 Pharmacodynamics

In a Phase 2 trial evaluating doravirine over a dose range of 0.25 to 2 times the recommended dose of PIFELTRO, (in combination with FTC/TDF) in participants living with HIV with no antiretroviral treatment history, no exposure-response relationship for efficacy was identified for doravirine.

Cardiac Electrophysiology

At a doravirine dose of 1200 mg, which provides approximately 4 times the peak concentration observed following the recommended dose of PIFELTRO, doravirine does not prolong the QT interval to any clinically relevant extent.

12.3 Pharmacokinetics

Doravirine pharmacokinetics are similar in healthy participants and participants living with HIV. Doravirine pharmacokinetics are provided in Table 7.

Table 7: Pharmacokinetic Properties of Doravirine
Parameter | Doravirine
General
Steady State Exposure [Doravirine 100 mg once daily to participants living with HIV] , [Presented as geometric mean (%CV: geometric coefficient of variation)]
AUC0-24 (mcg∙h/mL) | 16.1 (29)
Cmax (mcg/mL) | 0.962 (19)
C24 (mcg/mL) | 0.396 (63)
Time to Steady State (Days) | 2
Accumulation Ratio | 1.2 to 1.4
Absorption
Absolute Bioavailability | 64%
Tmax (h) | 2
Effect of Food [Geometric mean ratio [high-fat meal/fasting] and (90% confidence interval) for PK parameters. High fat meal is approximately 1,000 kcal, 50% fat. The effect of food is not clinically relevant.]
AUC Ratio | 1.16 (1.06, 1.26)
Cmax Ratio | 1.03 (0.89, 1.19)
C24 Ratio | 1.36 (1.19, 1.55)
Distribution
Vdss (L) [Based on IV dose] | 60.5
Plasma Protein Binding | 76%
Elimination
t1/2 (h) | 15
CL/F (mL/min) | 106 (35.2)
CLrenal (mL/min) | 9.3 (18.6)
Metabolism
Primary Pathway(s) | CYP3A
Excretion
Major Route of Elimination | Metabolism
Urine (unchanged) | 6%
Biliary/Fecal (unchanged) | Minor
Abbreviations: AUC=area under the time concentration curve; Cmax=maximum concentration; C24=concentration at 24 hours; Tmax time to Cmax; Vdss= volume of distribution at steady state, t1/2=elimination half-life; CL/F=apparent clearance; CLrenal=apparent renal clearance

Specific Populations

In adults, no clinically significant difference on the pharmacokinetics of doravirine were observed based on age (18 to 78 years of age), sex, and race/ethnicity, mild to severe renal impairment (creatinine clearance (CLcr) >15 mL/min, estimated by Cockcroft-Gault), or moderate hepatic impairment (Child-Pugh B). The pharmacokinetics of doravirine in patients with end-stage renal disease or undergoing dialysis, or severe hepatic impairment (Child-Pugh C) is unknown.

Patients with Renal Impairment

In a study comparing 8 participants with severe renal impairment to 8 participants without renal impairment, the single dose exposure of doravirine was 43% higher in participants with severe renal impairment. In a population pharmacokinetic analysis, renal function did not have a clinically relevant effect on doravirine pharmacokinetics. Doravirine has not been studied in patients with end-stage renal disease or in patients undergoing dialysis [see Use in Specific Populations (8.6)].

Patients with Hepatic Impairment

No clinically significant difference in the pharmacokinetics of doravirine was observed in participants with moderate hepatic impairment (Child-Pugh score B) compared to participants without hepatic impairment. Doravirine has not been studied in participants with severe hepatic impairment (Child-Pugh score C) [see Use in Specific Populations (8.7)].

Pediatric Patients

Mean doravirine exposures were similar in 54 pediatric participants aged 12 to less than 18 years and weighing at least 35 kg who received doravirine or DELSTRIGO in IMPAACT 2014 (Protocol 027) relative to adults following administration of doravirine or DELSTRIGO (Table 8). For pediatric participants weighing ≥ 35 kg and < 45 kg who received doravirine 100 mg or DELSTRIGO, the population pharmacokinetic model-predicted mean C24 of doravirine was comparable to that achieved in adults, whereas mean AUC0-24 and Cmax of doravirine were 25% and 36% higher than adult values, respectively. However, the predicted AUC0-24 and Cmax increases are not considered clinically significant.

Table 8: Steady State Pharmacokinetics for Doravirine Following Administration of Doravirine or DELSTRIGO in Pediatric Participants Living with HIV Aged 12 to Less than 18 Years and Weighing at Least 35 kg
Parameter [Presented as geometric mean (%CV: geometric coefficient of variation)] | Doravirine [From population PK analysis (n=53 weighing ≥45 kg, n=1 weighing ≥35 kg to <45 kg)]
AUC0-24 (mcg∙h/mL) | 16.4 (24)
Cmax (mcg/mL) | 1.03 (16)
C24 (mcg/mL) | 0.379 (42)
Abbreviations: AUC=area under the time concentration curve; Cmax=maximum concentration; C24=concentration at 24 hours

Drug Interaction Studies

Doravirine is primarily metabolized by CYP3A, and drugs that induce or inhibit CYP3A may affect the clearance of doravirine. Co-administration of doravirine and drugs that induce CYP3A may result in decreased plasma concentrations of doravirine. Co-administration of doravirine and drugs that inhibit CYP3A may result in increased plasma concentrations of doravirine.

Doravirine is not likely to have a clinically relevant effect on the exposure of medicinal products metabolized by CYP enzymes. Doravirine did not inhibit major drug metabolizing enzymes in vitro, including CYPs 1A2, 2B6, 2C8, 2C9, 2C19, 2D6, 3A4, and UGT1A1 and is not likely to be an inducer of CYP1A2, 2B6, or 3A4. Based on in vitro assays, doravirine is not likely to be an inhibitor of OATP1B1, OATP1B3, P-glycoprotein, BSEP, OAT1, OAT3, OCT2, MATE1, and MATE2K. Drug interaction studies were performed with doravirine and other drugs likely to be co-administered or commonly used as probes for pharmacokinetic interactions. The effects of co-administration with other drugs on the exposure (Cmax, AUC, and C24) of doravirine are summarized in Table 9. A single doravirine 100 mg dose was administered in these studies unless otherwise noted.

Table 9: Drug Interactions: Changes in Pharmacokinetic Parameter Values of Doravirine in the Presence of Co-administered Drug
Co-administered Drug | Regimen of Co-administered Drug | N | Geometric Mean Ratio (90% CI) of Doravirine Pharmacokinetics with/without Co-administered Drug (No Effect=1.00)
Co-administered Drug | Regimen of Co-administered Drug | N | AUC [AUC0-∞ for single-dose, AUC0-24 for once daily.] | Cmax | C24
Azole Antifungal Agents
ketoconazole [Changes in doravirine pharmacokinetic values are not clinically relevant.] | 400 mg QD | 10 | 3.06 (2.85, 3.29) | 1.25 (1.05, 1.49) | 2.75 (2.54, 2.98)
Antimycobacterials
rifampin | 600 mg QD | 10 | 0.12 (0.10, 0.15) | 0.43 (0.35, 0.52) | 0.03 (0.02, 0.04)
rifabutin | 300 mg QD | 12 | 0.50 (0.45, 0.55) | 0.99 (0.85, 1.15) | 0.32 (0.28, 0.35)
rifabutin | 300 mg QD [Doravirine 100 mg BID resulted in similar pharmacokinetic values when compared to 100 mg QD without rifabutin.] | 15 | 1.03 (0.94, 1.14) | 0.97 (0.87, 1.08) | 0.98 (0.88, 1.10)
HIV Antiviral Agents
ritonavir, [A single doravirine 50 mg dose (0.5 times the recommended approved dose) was administered.] | 100 mg BID | 8 | 3.54 (3.04, 4.11) | 1.31 (1.17, 1.46) | 2.91 (2.33, 3.62)
efavirenz | 600 mg QD [The first day following the cessation of efavirenz therapy and initiation of doravirine 100 mg QD.] | 17 | 0.38 (0.33, 0.45) | 0.65 (0.58, 0.73) | 0.15 (0.10, 0.23)
efavirenz | 600 mg QD [14 days following the cessation of efavirenz therapy and initiation of doravirine 100 mg QD.] | 17 | 0.68 (0.58, 0.80) | 0.86 (0.77, 0.97) | 0.50 (0.39, 0.64)
CI = confidence interval; QD = once daily; BID = twice daily

Based on drug interaction studies conducted with doravirine, no clinically significant drug interactions have been observed following the co-administration of doravirine and the following drugs: dolutegravir, ritonavir, TDF, lamivudine, elbasvir and grazoprevir, ledipasvir and sofosbuvir, ketoconazole, aluminum hydroxide/magnesium hydroxide/simethicone containing antacid, pantoprazole, atorvastatin, an oral contraceptive containing ethinyl estradiol and levonorgestrel, metformin, methadone, and midazolam.

12.4 Microbiology

Mechanism of Action

Doravirine is a pyridinone non-nucleoside reverse transcriptase inhibitor of HIV-1 and inhibits HIV-1 replication by non-competitive inhibition of HIV-1 reverse transcriptase (RT). The inhibitory concentration at 50% (IC50) of doravirine for RNA-dependent DNA polymerization of recombinant wild-type HIV-1 RT in a biochemical assay was 12.2±2.0 nM (n=3). Doravirine does not inhibit the human cellular DNA polymerases α, β, and mitochondrial DNA polymerase γ.

Antiviral Activity in Cell Culture

Doravirine exhibited an EC50 value of 12.0±4.4 nM against wild-type laboratory strains of HIV-1 when tested in the presence of 100% normal human serum (NHS) using MT4-GFP reporter cells and a median EC50 value for HIV-1 subtype B primary isolates (n=118) of 4.1 nM (range: 1.0 nM-16.0 nM). Doravirine demonstrated antiviral activity against a broad panel of primary HIV-1 isolates (A, A1, AE, AG, B, BF, C, D, G, H) with EC50 values ranging from 1.2 nM to 10.0 nM.

Antiviral Activity in Combination with other HIV Antiviral Agents

The antiviral activity of doravirine in cell culture was not antagonistic when combined with the NNRTIs delavirdine, efavirenz, etravirine, nevirapine, or rilpivirine; the NRTIs abacavir, didanosine, emtricitabine, lamivudine, stavudine, tenofovir DF, or zidovudine; the PIs darunavir or indinavir; the gp41 fusion inhibitor enfuvirtide; the CCR5 co-receptor antagonist maraviroc; or the integrase strand transfer inhibitor raltegravir.

Resistance

In Cell Culture

Doravirine-resistant strains were selected in cell culture starting from wild-type HIV-1 of different origins and subtypes, as well as NNRTI-resistant HIV-1. Observed emergent amino acid substitutions in RT included: V106A, V106I, V106M, V108I, H221Y, F227C, F227I, F227L, F227V, M230I, L234I, P236L, and Y318F. The V106A, V106M, V108I, H221Y, F227C, M230I, P236L, and Y318F substitutions conferred 3.4-fold to 70-fold reductions in susceptibility to doravirine. Y318F in combination with V106A, V106M, V108I, or F227C conferred greater decreases in susceptibility to doravirine than Y318F alone, which conferred a 10-fold reduction in susceptibility to doravirine.

In Clinical Trials

Clinical Trial Results in Adults with No Antiretroviral Treatment History

In the doravirine treatment arms of the DRIVE-FORWARD and DRIVE-AHEAD trials (n=747) through Week 96, 13 participants showed the emergence of doravirine resistance-associated substitutions in their HIV among 36 (36%) participants in the resistance analysis subset (participants with HIV-1 RNA greater than 400 copies per mL at virologic failure or early study discontinuation and having post-baseline resistance samples). Emergent doravirine resistance-associated substitutions in RT included one or more of the following: V90G/I, A98G, V106A, V106I, V106M/T, V108I, E138G, Y188L, H221Y, P225H, P225L, P225P/S, F227C, F227C/R, Y318Y/F and Y318Y/S. Eight of 13 (62%) participants with emergent doravirine resistance-associated substitutions showed doravirine phenotypic resistance and most of them had at least a 100-fold reduction in doravirine susceptibility (range >95- to >211–fold reduction in doravirine susceptibility). The other 5 virologic failures who had only amino acid mixtures of NNRTI resistance substitutions showed doravirine phenotypic fold-changes of less than 2-fold. Of the 36 participants in the resistance analysis subset, 10 participants (28%) developed genotypic and/or phenotypic resistance to the other drugs (abacavir, emtricitabine, lamivudine, or tenofovir) in the regimens of the DRIVE-FORWARD and DRIVE-AHEAD trials. The resistance-associated substitutions that emerged were RT M41L (n=1), A62A/V (n=1), K65R (n=2), T69T/A (n=1), V75V/I (n=1), and M184I or V (n=7).

In the DRV/r treatment arm of the DRIVE-FORWARD trial (n=383) through Week 96, no participants showed the emergence of darunavir resistance-associated substitutions among 15 participants with resistance data and 2 of the participants had emergent genotypic or phenotypic resistance to lamivudine or tenofovir. In the EFV/FTC/TDF treatment arm of the DRIVE-AHEAD trial (n=364) through Week 96, 15 participants showed the emergence of efavirenz resistance-associated substitutions among 25 (60%) participants in the resistance analysis subset and genotypic resistance to emtricitabine or tenofovir developed in 5 evaluable participants; emergent resistance-associated substitutions were RT K65R (n=1), D67G/K70E (n=1), L74V/V75M/V118I (n=1), M184I or V (n=5), and K219K/E (n=1).

Clinical Trial Results in Virologically-Suppressed Adults

In the DRIVE-SHIFT clinical trial [see Clinical Studies (14.2)], there were 6 participants in the immediate switch group (n=447) and 2 participants in the delayed switch group (n=209) who met the protocol-defined virologic failure criteria (confirmed HIV-1 RNA ≥ 50 copies/mL). Two of the 6 virologic failure participants in the immediate switch group had available resistance data and neither developed detectable genotypic or phenotypic resistance to doravirine, lamivudine, or tenofovir during treatment with DELSTRIGO. One of the two virologic failure participants in the delayed switch group who had available resistance data developed the RT M184M/I substitution and phenotypic resistance to emtricitabine and lamivudine during treatment with their baseline regimen.

Cross-Resistance

Cross-resistance has been observed among NNRTIs. Treatment-emergent doravirine resistance-associated substitutions can confer cross-resistance to efavirenz, etravirine, nevirapine, and rilpivirine. Of the 8 virologic failure participants who developed doravirine phenotypic resistance, all had phenotypic resistance to nevirapine, 6 had phenotypic resistance to efavirenz, 4 had phenotypic resistance to rilpivirine, and 4 had resistance to etravirine in the Monogram PhenoSense assay. Of the 11 virologic failure participants in DRIVE-AHEAD phenotypically resistant to efavirenz, 2 (18%) had decreased susceptibility to doravirine (18- and 36-fold).

The treatment-emergent doravirine resistance-associated substitution Y318F did not confer reduced susceptibility to efavirenz, etravirine, or rilpivirine.

A panel of 96 diverse clinical isolates containing NNRTI resistance-associated substitutions was evaluated for susceptibility to doravirine. Clinical isolates containing the Y188L substitution alone or in combination with K103N or V106I, V106A in combination with G190A and F227L, or E138K in combination with Y181C and M230L showed greater than 100-fold reduced susceptibility to doravirine.

13 NONCLINICAL TOXICOLOGY

13.1 Carcinogenesis, Mutagenesis, Impairment of Fertility

Carcinogenesis

Doravirine was not carcinogenic in long-term oral carcinogenicity studies in mice and rats at exposures up to 6 and 7 times, respectively, the human exposures at the RHD. A statistically significant incidence of thyroid parafollicular cell adenoma and carcinoma seen only in female rats at the high dose was within the range observed in historical controls.

Mutagenesis

Doravirine was not genotoxic in a battery of in vitro or in vivo assays, including microbial mutagenesis, chromosomal aberration in Chinese hamster ovary cells, and in in vivo rat micronucleus assays.

Impairment of fertility

There were no effects on fertility, mating performance or early embryonic development when doravirine was administered to rats at systemic exposures (AUC) approximately 7 times the exposure in humans at the RHD.

14 CLINICAL STUDIES

14.1 Clinical Trial Results in Adults with No Antiretroviral Treatment History

The efficacy of PIFELTRO is based on the analyses of 96-week data from two randomized, multicenter, double-blind, active controlled Phase 3 trials (DRIVE-FORWARD, NCT02275780 and DRIVE-AHEAD, NCT02403674) in participants living with HIV with no antiretroviral treatment history (n=1494).

In DRIVE-FORWARD, 766 participants were randomized and received at least 1 dose of either PIFELTRO once daily or darunavir 800 mg + ritonavir 100 mg (DRV+r) once daily each in combination with emtricitabine/tenofovir DF (FTC/TDF) or abacavir/lamivudine (ABC/3TC) selected by the investigator. At baseline, the median age of participants was 33 years, 16% were female, 27% were Non-White, 4% had hepatitis B and/or C virus co-infection, 10% had a history of AIDS, 20% had HIV-1 RNA greater than 100,000 copies/mL, 86% had CD4+ T-cell count greater than 200 cells/mm^3, 13% received ABC/3TC, and 87% received FTC/TDF; these characteristics were similar between treatment groups.

In DRIVE-AHEAD, 728 participants were randomized and received at least 1 dose of either DELSTRIGO (DOR/3TC/TDF) or EFV 600 mg/FTC 200 mg/TDF 300 mg once daily. At baseline, the median age of participants was 31 years, 15% were female, 52% were Non-White, 3% had hepatitis B or C co-infection, 14% had a history of AIDS, 21% had HIV-1 RNA greater than 100,000 copies/mL, and 88% had CD4+ T-cell count greater than 200 cells/mm^3; these characteristics were similar between treatment groups.

Week 96 outcomes for DRIVE-FORWARD and DRIVE-AHEAD are provided in Table 10. Side-by-side tabulation is to simplify presentation; direct comparisons across trials should not be made due to differing trial designs.

In DRIVE-FORWARD, the mean CD4+ T-cell counts in the PIFELTRO and DRV+r groups increased from baseline by 224 and 207 cells/mm^3, respectively.

In DRIVE-AHEAD, the mean CD4+ T-cell counts in the DELSTRIGO and EFV/FTC/TDF groups increased from baseline by 238 and 223 cells/mm^3, respectively.

Table 10: Virologic Outcome in DRIVE-FORWARD and DRIVE-AHEAD at Week 96 in HIV-1 Adults with No Antiretroviral Treatment History
Outcome | DRIVE-FORWARD |  | DRIVE-AHEAD
Outcome | PIFELTRO + 2 NRTIs Once Daily | DRV+r + 2 NRTIs Once Daily | DELSTRIGO Once Daily | EFV/FTC/TDF Once Daily
Outcome | N=383 | N=383 | N=364 | N=364
HIV-1 RNA <50 copies/mL | 72% | 65% | 77% | 74%
Treatment Differences (95% CI) [The 95% CIs for the treatment differences were calculated using stratum-adjusted Mantel-Haenszel method.] | 7.5% (1.0%, 14.1%) |  | 3.8% (-2.4%, 10.0%)
HIV-1 RNA ≥ 50 copies/mL [Includes participants who discontinued study drug or study before Week 96 for lack or loss of efficacy and participants with HIV-1 RNA equal to or above 50 copies/mL in the Week 96 window.] | 17% | 20% | 15% | 12%
No Virologic Data at Week 96 Window | 11% | 15% | 7% | 14%
Discontinued study due to AE or Death [Includes participants who discontinued because of adverse event (AE) or death if this resulted in no virologic data in the Week 96 window.] | 2% | 4% | 3% | 8%
Discontinued study for Other Reasons [Other Reasons include: lost to follow-up, non-compliance with study drug, physician decision, pregnancy, protocol deviation, screen failure, withdrawal by participant.] | 7% | 9% | 4% | 5%
On study but missing data in window | 2% | 3% | 1% | 1%
Proportion (%) of Participants With HIV-1 RNA <50 copies/mL at Week 96 by Baseline and Demographic Category
Gender
Male | 72% (N = 319) | 67% (N = 326) | 78% (N = 305) | 73% (N = 311)
Female | 73% (N = 64) | 54% (N = 57) | 75% (N = 59) | 75% (N = 53)
Race
White | 78% (N = 280) | 68% (N = 280) | 80% (N = 176) | 74% (N = 170)
Non-White | 58% (N = 103) | 57% (N = 102) | 76% (N = 188) | 74% (N = 194)
Ethnicity [Does not include participants whose ethnicity or viral subtypes were unknown.]
Hispanic or Latino | 76% (N = 93) | 63% (N = 86) | 81% (N = 126) | 77% (N = 119)
Not Hispanic or Latino | 71% (N = 284) | 66% (N = 290) | 76% (N = 238) | 72% (N = 239)
NRTI Background Therapy
FTC/TDF | 71% (N = 333) | 64% (N = 335) | - | -
ABC/3TC | 80% (N = 50) | 67% (N = 48) | - | -
Baseline HIV-1 RNA (copies/mL)
≤100,000 copies/mL | 75% (N = 300) | 66% (N = 309) | 80% (N = 291) | 77% (N = 282)
>100,000 copies/mL | 61% (N = 83) | 59% (N = 73) | 67% (N = 73) | 62% (N = 82)
CD4+ T-cell Count (cells/mm^3)
≤200 cells/mm^3 | 62% (N = 42) | 51% (N = 67) | 59% (N = 44) | 70% (N = 46)
>200 cells/mm^3 | 74% (N = 341) | 68% (N = 316) | 80% (N = 320) | 74% (N = 318)
Viral Subtype
Subtype B | 71% (N = 266) | 66% (N = 272) | 80% (N = 232) | 72% (N = 253)
Subtype Non-B | 75% (N = 117) | 62% (N = 111) | 73% (N = 130) | 77% (N = 111)
Note: NRTIs = FTC/TDF or ABC/3TC.

14.2 Clinical Trial Results in Virologically-Suppressed Adults

The efficacy of switching from a baseline regimen consisting of two NRTIs in combination with a PI plus either ritonavir or cobicistat, or elvitegravir plus cobicistat, or an NNRTI to DELSTRIGO was evaluated in a randomized, open-label trial (DRIVE-SHIFT, NCT02397096), in virologically-suppressed adults living with HIV. Participants must have been virologically-suppressed (HIV-1 RNA < 50 copies/mL) on their baseline regimen for at least 6 months prior to trial entry, with no history of virologic failure. Participants were randomized to either switch to DELSTRIGO at baseline (n = 447, Immediate Switch Group (ISG)), or stay on their baseline regimen until Week 24, at which point they switched to DELSTRIGO (n = 223, Delayed Switch Group (DSG)).

At baseline, the median age of participants was 43 years, 16% were female, and 24% were Non-White, 21% were of Hispanic or Latino ethnicity, 3% had hepatitis B and/or C virus co-infection, 17% had a history of AIDS, 96% had CD4+ T-cell count greater than or equal to 200 cells/mm^3, 70% were on a regimen containing a PI plus ritonavir, 24% were on a regimen containing an NNRTI, 6% were on a regimen containing elvitegravir plus cobicistat, and 1% were on a regimen containing a PI plus cobicistat; these characteristics were similar between treatment groups.

Virologic outcome results are shown in Table 11.

Table 11: Virologic Outcomes in DRIVE-SHIFT in HIV-1 Virologically-Suppressed Participants Who Switched to DELSTRIGO
Outcome | DELSTRIGO Once Daily ISG Week 48 N=447 | Baseline Regimen DSG Week 24 N=223
HIV-1 RNA ≥ 50 copies/mL [Includes participants who discontinued study drug or study before Week 48 for ISG or before Week 24 for DSG for lack or loss of efficacy and participants with HIV-1 RNA ≥50 copies/mL in the Week 48 window for ISG and in the Week 24 window for DSG.] | 2% | 1%
ISG-DSG, Difference (95% CI) [The 95% CI for the treatment difference was calculated using stratum-adjusted Mantel-Haenszel method.] , [Assessed using a non-inferiority margin of 4%.] | 0.7% (-1.3%, 2.6%)
HIV-1 RNA <50 copies/mL | 91% | 95%
No Virologic Data Within the Time Window | 8% | 4%
Discontinued study due to AE or Death [Includes participants who discontinued because of adverse event (AE) or death if this resulted in no virologic data on treatment during the specified window.] | 3% | <1%
Discontinued study for Other Reasons [Other reasons include: lost to follow-up, non-compliance with study drug, physician decision, protocol deviation, withdrawal by participant.] | 4% | 4%
On study but missing data in window | 0 | 0
Proportion (%) of Participants With HIV-1 RNA <50 copies/mL by Baseline and Demographic Category
Age (years)
< 50 | 90% (N = 320) | 95% (N = 157)
≥ 50 | 94% (N = 127) | 94% (N = 66)
Gender
Male | 91% (N = 372) | 94% (N = 194)
Female | 91% (N = 75) | 100% (N = 29)
Race
White | 90% (N = 344) | 95% (N = 168)
Non-White | 93% (N = 103) | 93% (N = 55)
Ethnicity
Hispanic or Latino | 88% (N = 99) | 91% (N = 45)
Not Hispanic or Latino | 91% (N = 341) | 95% (N = 175)
CD4+ T-cell Count (cells/mm^3)
<200 cells/mm^3 | 85% (N = 13) | 75% (N = 4)
≥200 cells/mm^3 | 91% (N = 426) | 95% (N = 216)
Baseline Regimen [Baseline Regimen = PI plus either ritonavir or cobicistat (specifically atazanavir, darunavir, or lopinavir), or elvitegravir plus cobicistat, or NNRTI (specifically efavirenz, nevirapine, or rilpivirine), each administered with two NRTIs.]
PI plus either ritonavir or cobicistat | 90% (N=316) | 94% (N=156)
elvitegravir plus cobicistat or NNRTI | 93% (N=131) | 96% (N=67)

14.3 Clinical Trial Results in Pediatric Participants

The efficacy of DELSTRIGO (DOR/3TC/TDF) was evaluated in cohort 2 of an open-label, single-arm 2-cohort trial in pediatric participants 12 to less than 18 years of age living with HIV (IMPAACT 2014 (Protocol 027), NCT03332095). In cohort 1, virologically-suppressed participants (n=9) received a single 100 mg dose of PIFELTRO followed by intensive PK sampling. In cohort 2, virologically-suppressed participants (n=43) were switched to DELSTRIGO and treatment-naïve participants (n=2) were started on DELSTRIGO.

In cohort 2, at baseline the median age of participants was 15 years (range: 12 to 17), the median weight was 52 kg (range: 45 to 80), 58% were female, 78% were Asian and 22% were Black, and the median CD4+ T-cell count was 713 cells per mm^3 (range 84 to 1397). After switching to DELSTRIGO, 95% (41/43) of virologically-suppressed participants remained suppressed (HIV-1 RNA <50 copies/mL) at Week 24. One of the two treatment-naïve participants achieved HIV-1 RNA <50 copies/mL at Week 24. The other treatment-naïve participant met the protocol-defined virologic failure criteria (defined as 2 consecutive plasma HIV-1 RNA test results ≥200 copies/mL at or after Week 24) and was evaluated for the development of resistance; no emergence of genotypic or phenotypic resistance to doravirine, lamivudine, or tenofovir was detected.

16 HOW SUPPLIED/STORAGE AND HANDLING

Each PIFELTRO tablet contains 100 mg of doravirine, is white, oval-shaped and film-coated, and is debossed with the corporate logo and 700 on one side and plain on the other side. Each bottle contains 30 tablets (NDC 0006-3069-01) with silica gel desiccant and is closed with a child-resistant closure.

STORAGE AND HANDLING

Store PIFELTRO in the original bottle. Keep the bottle tightly closed to protect from moisture. Do not remove the desiccant.

Store PIFELTRO at 20°C to 25°C (68°F to 77°F); excursions permitted to 15°C to 30°C (59°F to 86°F) [see USP Controlled Room Temperature].

17 PATIENT COUNSELING INFORMATION

Advise the patient to read the FDA-approved patient labeling (Patient Information).

Severe Skin Reactions

Inform patients that severe skin reactions including Stevens-Johnson syndrome (SJS)/toxic epidermal necrolysis (TEN) have been reported with PIFELTRO. Advise patients to immediately contact their healthcare provider if they develop a rash. Instruct patients to immediately stop taking PIFELTRO and seek medical attention if a painful rash with mucosal involvement develops [see Warnings and Precautions (5.1)].

Drug Interactions

Inform patients that PIFELTRO may interact with certain other drugs; therefore, advise patients to report to their healthcare provider the use of any other prescription or nonprescription medication or herbal products, including St. John's wort [see Contraindications (4), Warnings and Precautions (5.2), and Drug Interactions (7.1)].

For patients concomitantly receiving rifabutin, take one tablet of PIFELTRO twice daily (approximately 12 hours apart) [see Dosage and Administration (2.2)].

Immune Reconstitution Syndrome

Inform patients that in some patients with advanced HIV infection (AIDS), signs and symptoms of inflammation from previous infections may occur soon after anti-HIV treatment is started. It is believed that these symptoms are due to an improvement in the body's immune response, enabling the body to fight infections that may have been present with no obvious symptoms. Advise patients to inform their healthcare provider immediately of any symptoms of infection [see Warnings and Precautions (5.3)].

Dosing Instructions

Advise patients to take PIFELTRO every day at a regularly scheduled time with or without food. Inform patients that it is important not to miss or skip doses as it can result in development of resistance. If a patient forgets to take PIFELTRO, tell the patient to take the missed dose right away, unless it is almost time for the next dose. Advise the patient not to take 2 doses at one time and to take the next dose at the regularly scheduled time.

Pregnancy Registry

Inform patients that there is an antiretroviral pregnancy registry to monitor fetal outcomes in pregnant individuals exposed to PIFELTRO [see Use in Specific Populations (8.1)].

Lactation

Inform individuals with HIV-1 infection that the potential risks of breastfeeding include: (1) HIV-1 transmission (in HIV-1–negative infants), (2) developing viral resistance (in HIV-1– positive infants), and (3) serious adverse reactions in a breastfed infant similar to those seen in adults [see Use in Specific Populations (8.2)].

Manufactured for: Merck Sharp & Dohme LLC
Rahway, NJ 07065, USA

For patent information: www.msd.com/research/patent

The trademarks depicted herein are owned by their respective companies.

Copyright © 2018-2025 Merck & Co., Inc., Rahway, NJ, USA, and its affiliates.
All rights reserved.

uspi-mk1439-t-2510r008

Patient Information
PIFELTRO® (pih-FEL-tro)
(doravirine)
tablets

What is PIFELTRO?

PIFELTRO is a prescription medicine that is used together with other HIV-1 medicines to treat Human Immunodeficiency Virus-1 (HIV-1) infection in adults and children who weigh at least 77 pounds (35 kg):

- who have not received HIV-1 medicines in the past, or
- to replace their current HIV-1 medicines for people whose healthcare provider determines that they meet certain requirements.

HIV-1 is the virus that causes Acquired Immune Deficiency Syndrome (AIDS).
It is not known if PIFELTRO is safe and effective in children who weigh less than 77 pounds (35 kg).
Who should not take PIFELTRO?

Do not take PIFELTRO if you take any of the following medicines:

- carbamazepine
- oxcarbazepine
- phenobarbital
- phenytoin
- enzalutamide

- rifampin
- rifapentine
- mitotane
- St. John's wort

Ask your healthcare provider or pharmacist if you are not sure if your medicine is one that is listed above. If you have taken any of the medicines in the past 4 weeks, talk to your healthcare provider or pharmacist before starting treatment with PIFELTRO.
What should I tell my healthcare provider before treatment with PIFELTRO?

Before treatment with PIFELTRO, tell your healthcare provider about all of your medical conditions, including if you:

- are pregnant or plan to become pregnant. It is not known if PIFELTRO can harm your unborn baby. Tell your healthcare provider if you become pregnant during treatment with PIFELTRO.
  Pregnancy Registry: There is a pregnancy registry for people who take PIFELTRO during pregnancy. The purpose of this registry is to collect information about the health of you and your baby. Talk to your healthcare provider about how you can take part in this registry.
- are breastfeeding or plan to breastfeed. PIFELTRO may pass to your baby in your breast milk. Talk with your healthcare provider about the following risks to your baby from breastfeeding during treatment with PIFELTRO:
  - the HIV-1 virus may pass to your baby if your baby does not have HIV-1 infection.
  - the HIV-1 virus may become harder to treat if your baby has HIV-1 infection.
  - your baby may get side effects from PIFELTRO.

Tell your healthcare provider about all the medicines you take, including prescription and over-the-counter medicines, vitamins, and herbal supplements.

- Some medicines interact with PIFELTRO. Keep a list of your medicines to show your healthcare provider and pharmacist.
- Tell your healthcare provider if you have taken rifabutin in the past 4 weeks.
- You can ask your healthcare provider or pharmacist for a list of medicines that interact with PIFELTRO.
- Do not start taking a new medicine without telling your healthcare provider. Your healthcare provider can tell you if it is safe to take PIFELTRO with other medicines.

How do I take PIFELTRO?

- Take PIFELTRO every day exactly as your healthcare provider tells you to take it.
- Take PIFELTRO 1 time each day, at about the same time every day.
- If you take the medicine rifabutin during treatment with PIFELTRO, take PIFELTRO 2 times each day, about 12 hours apart, as prescribed by your healthcare provider. You may not have enough doravirine in your blood if you take rifabutin during treatment with PIFELTRO.
- Take PIFELTRO with or without food.
- Do not change your dose or stop taking PIFELTRO without talking to your healthcare provider. Stay under a healthcare provider's care when taking PIFELTRO.
- It is important that you do not miss or skip doses of PIFELTRO.
- If you miss a dose of PIFELTRO, take it as soon as you remember. If it is almost time for your next dose, skip the missed dose and take the next dose at your regular time. Do not take 2 doses of PIFELTRO at the same time.
- If you have any questions, call your healthcare provider or pharmacist.
- When your PIFELTRO supply starts to run low, get more from your healthcare provider or pharmacy. This is very important because the amount of virus in your blood may increase if the medicine is stopped for even a short time. The virus may develop resistance to PIFELTRO and become harder to treat.

What are the possible side effects of PIFELTRO?

PIFELTRO can cause serious side effects, including:

- Severe skin reactions have happened in people treated with PIFELTRO. Call your healthcare provider right away if you develop a rash during treatment with PIFELTRO. Stop taking PIFELTRO and get medical help right away if you develop a painful rash with any of the following symptoms: fever, blisters or sores in the mouth, blisters or peeling of the skin, or redness or swelling of the eyes (conjunctivitis).
- Changes in your immune system (Immune Reconstitution Syndrome) can happen when you start taking HIV-1 medicines. Your immune system may get stronger and begin to fight infections that have been hidden in your body for a long time. Tell your healthcare provider right away if you start having any new symptoms after starting your HIV-1 medicine.

The most common side effects of PIFELTRO include:

- nausea
- dizziness
- headache
- tiredness

- diarrhea
- stomach (abdominal) pain
- abnormal dreams

These are not all of the possible side effects of PIFELTRO.
Call your doctor for medical advice about side effects. You may report side effects to FDA at 1-800-FDA-1088.
How should I store PIFELTRO?

- Store PIFELTRO tablets at room temperature between 68°F to 77°F (20°C to 25°C).
- Keep PIFELTRO in the original bottle.
- Do not take the tablets out of the bottle to store in another container, such as a pill box.
- Keep the bottle tightly closed to protect PIFELTRO from moisture.
- The PIFELTRO bottle contains a desiccant to help keep your medicine dry (protect it from moisture). Keep the desiccant in the bottle. Do not eat the desiccant.

Keep PIFELTRO and all medicines out of the reach of children.
General information about the safe and effective use of PIFELTRO.

Medicines are sometimes prescribed for purposes other than those listed in the Patient Information leaflet. Do not use PIFELTRO for a condition for which it was not prescribed. Do not give PIFELTRO to other people, even if they have the same symptoms that you have. It may harm them. You can ask your pharmacist or healthcare provider for information about PIFELTRO that is written for healthcare professionals.
What are the ingredients in PIFELTRO?

Active ingredient: doravirine.
Inactive ingredients: colloidal silicon dioxide, croscarmellose sodium, hypromellose acetate succinate, lactose monohydrate, magnesium stearate, and microcrystalline cellulose. The tablet film coating contains hypromellose, lactose monohydrate, titanium dioxide and triacetin. The coated tablets are polished with carnauba wax.

Manufactured for: Merck Sharp & Dohme LLC
Rahway, NJ 07065, USA

For patent information: www.msd.com/research/patent

The trademarks depicted herein are owned by their respective companies.

Copyright © 2018-2024 Merck & Co., Inc., Rahway, NJ, USA, and its affiliates.
All rights reserved.

usppi-mk1439-t-2411r005

For more information, go to www.PIFELTRO.com or call 1-877-888-4231.

This Patient Information has been approved by the U.S. Food and Drug Administration. Revised: 11/2024

PRINCIPAL DISPLAY PANEL - 100 mg Bottle Label

NDC 0006-3069-01

Pifeltro®
(doravirine) tablets

100 mg

Each tablet contains 100 mg doravirine.

ALERT: Find out about medicines that
should NOT be taken with Pifeltro®.

Rx only

30 Tablets